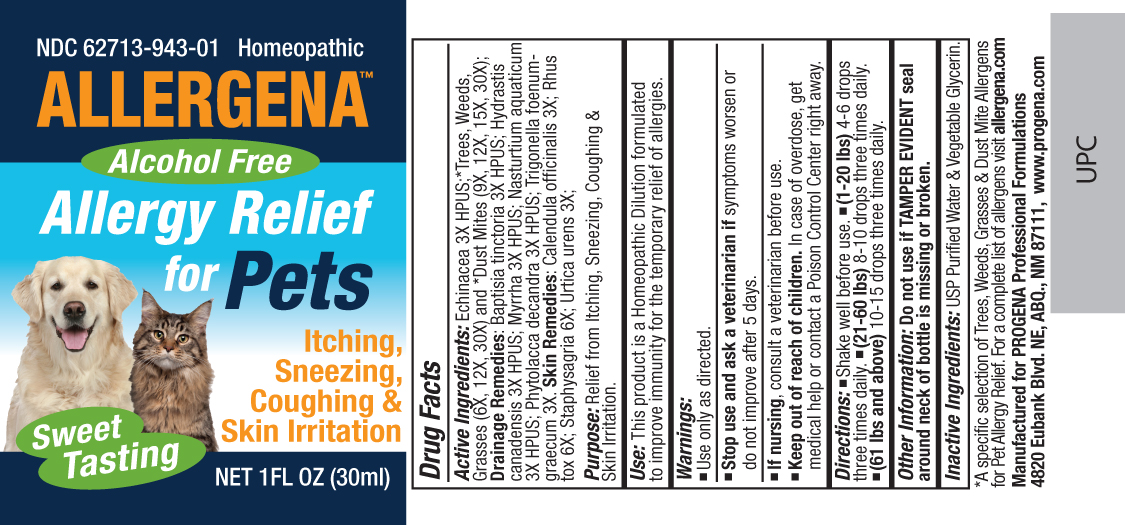 DRUG LABEL: Allergena for Pets
NDC: 62713-943 | Form: LIQUID
Manufacturer: Meditrend, Inc. DBA Progena Professional Formulations
Category: homeopathic | Type: HUMAN OTC DRUG LABEL
Date: 20121016

ACTIVE INGREDIENTS: ECHINACEA, UNSPECIFIED 3 [hp_X]/1 mL; BETULA PAPYRIFERA POLLEN 30 [hp_X]/1 mL; JUNIPERUS ASHEI POLLEN 30 [hp_X]/1 mL; QUERCUS RUBRA POLLEN 30 [hp_X]/1 mL; ARTEMISIA VULGARIS POLLEN 30 [hp_X]/1 mL; AMARANTHUS RETROFLEXUS POLLEN 30 [hp_X]/1 mL; AMBROSIA ARTEMISIIFOLIA POLLEN 30 [hp_X]/1 mL; SALSOLA TRAGUS POLLEN 30 [hp_X]/1 mL; PASPALUM NOTATUM POLLEN 30 [hp_X]/1 mL; CYNODON DACTYLON POLLEN 30 [hp_X]/1 mL; POA ANNUA POLLEN 30 [hp_X]/1 mL; LOLIUM PERENNE POLLEN 30 [hp_X]/1 mL; PHLEUM PRATENSE POLLEN 30 [hp_X]/1 mL; DERMATOPHAGOIDES PTERONYSSINUS 30 [hp_X]/1 mL; DERMATOPHAGOIDES FARINAE 30 [hp_X]/1 mL; BAPTISIA TINCTORIA ROOT 3 [hp_X]/1 mL; GOLDENSEAL 3 [hp_X]/1 mL; MYRRH 3 [hp_X]/1 mL; NASTURTIUM OFFICINALE 3 [hp_X]/1 mL; PHYTOLACCA AMERICANA ROOT 3 [hp_X]/1 mL; FENUGREEK LEAF 3 [hp_X]/1 mL; CALENDULA OFFICINALIS FLOWERING TOP 3 [hp_X]/1 mL; TOXICODENDRON PUBESCENS LEAF 6 [hp_X]/1 mL; DELPHINIUM STAPHISAGRIA SEED 6 [hp_X]/1 mL; URTICA URENS 3 [hp_X]/1 mL
INACTIVE INGREDIENTS: GLYCERIN; WATER

Allergena for Pets

ACTIVE INGREDIENT

Active Ingredients: Echinacea 3X HPUS;*Trees, Weeds, Grasses (6X, 12X, 30X) and *Dust Mites (9X, 12X, 15X, 30X); Drainage Remedies: Baptisia tinctoria 3X HPUS; Hydrastis canadensis 3X HPUS; Myrrha 3X HPUS; Nasturtium aquaticum 3X HPUS; Phytolacca decandra 3X HPUS; Trigonella foenum-graecum 3X. Skin Remedies: Calendula officinalis 3X; Rhus tox 6X; Staphysagria 6X; Urtica urens 3X;

PURPOSE

Purpose: Relief from Itching, Sneezing, Coughing and Skin Irritation.

Keep Out of Reach of Children. In case of overdose, get medical help or contact a
Poison Control Center right away.

INDICATIONS AND USAGE

Use: This product is a Homeopathic Dilution formulated to improve immunity for the temporary relief of allergies.

Warnings:

- Use Only as directed.
- Stop use and ask a veterinarian ifsymptoms worsen or do not improve after 5 days.
- If nursing,, consult a veterinarian before use.

DOSAGE AND ADMINISTRATION

Directions:•Shake Well Before Use.•(1-20 lbs)4-6 drops three times daily.•(21-60 lbs)8-10 drops three times daily.•(61 lbs and above) 10-15 drops three times daily.10-15 drops three times daily.

Other Information: Do not use if TAMPER EVIDENT seal around neck of bottle is missing or broken.

Inactive Ingredients: USP Purified Water and Vegetable Glycerin.

PACKAGE LABEL

Manufactured for Progena Professional Formulations
4820 Eubank Blvd. NE, ABQ, NM 87111, www.progena.com